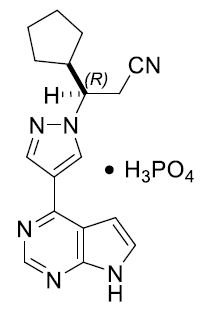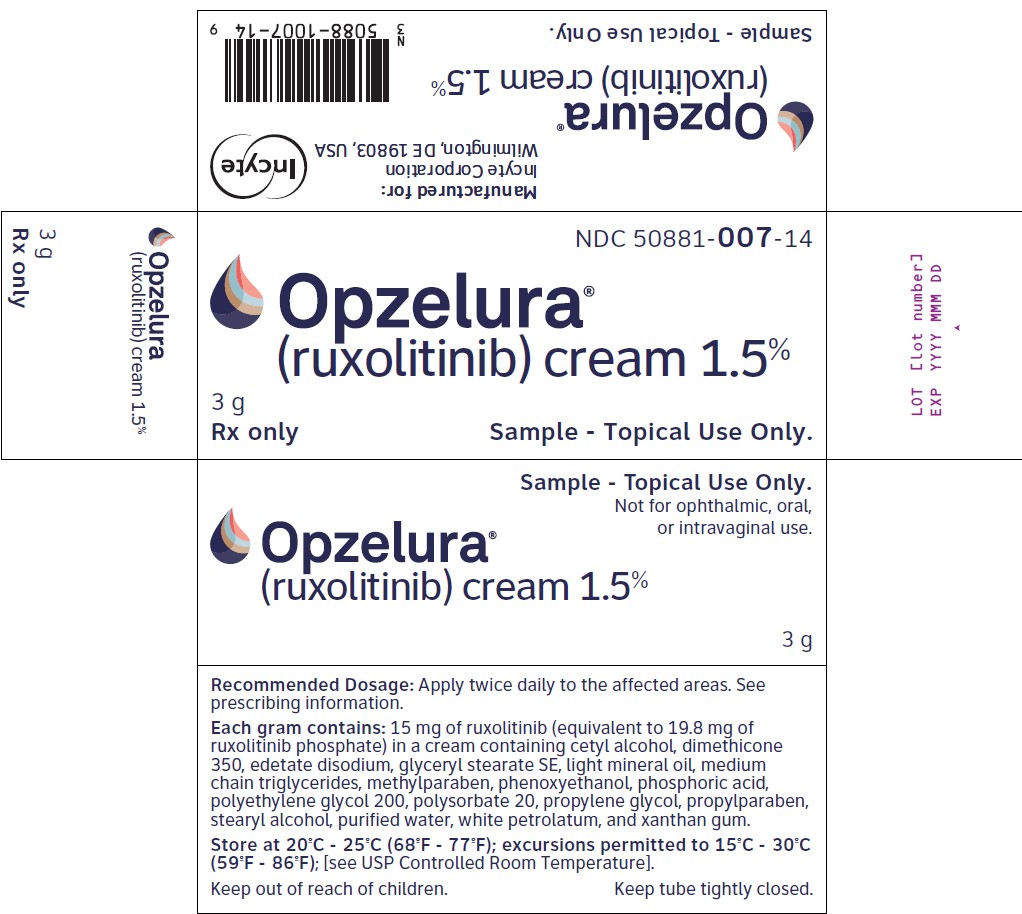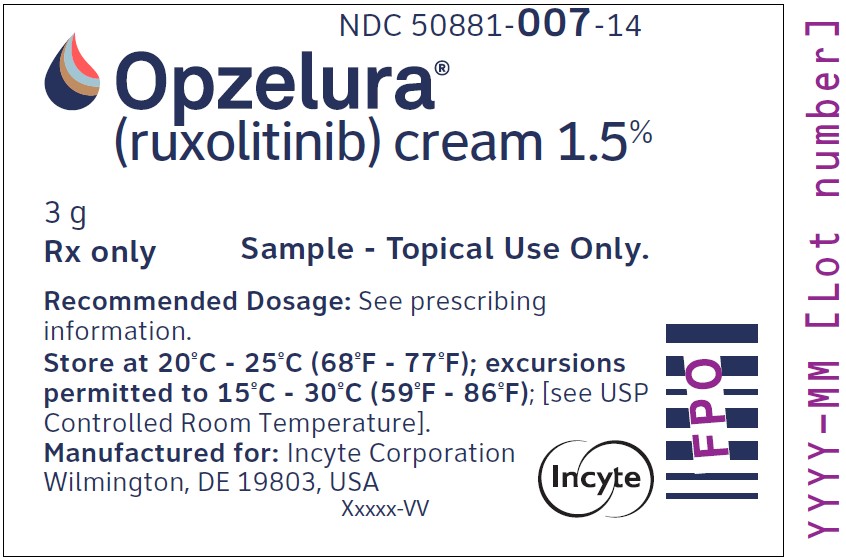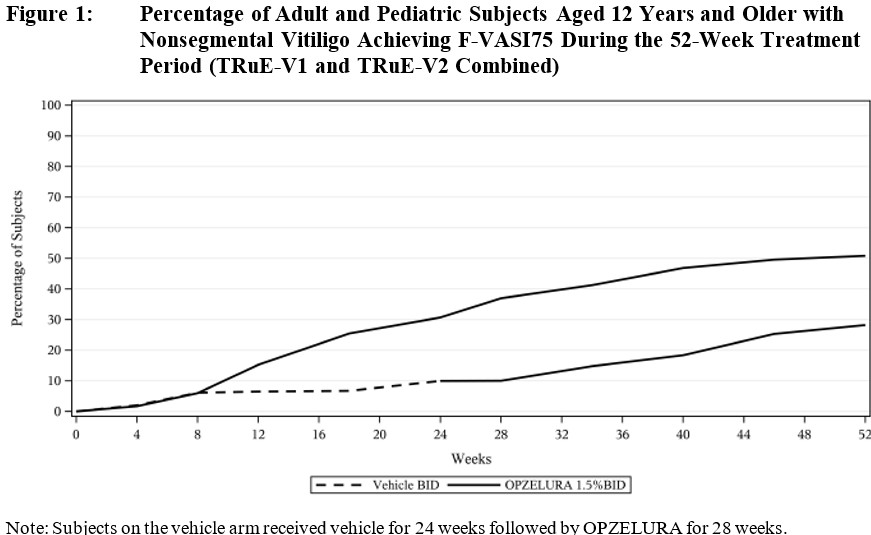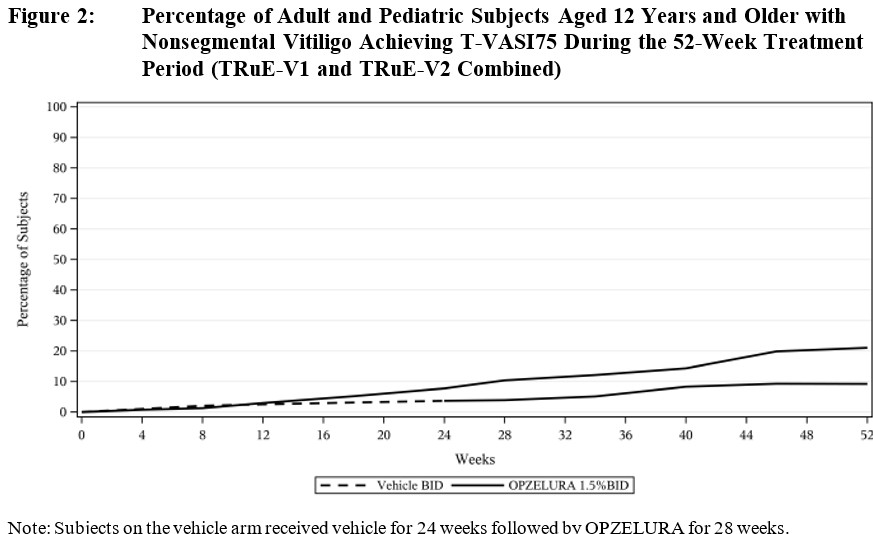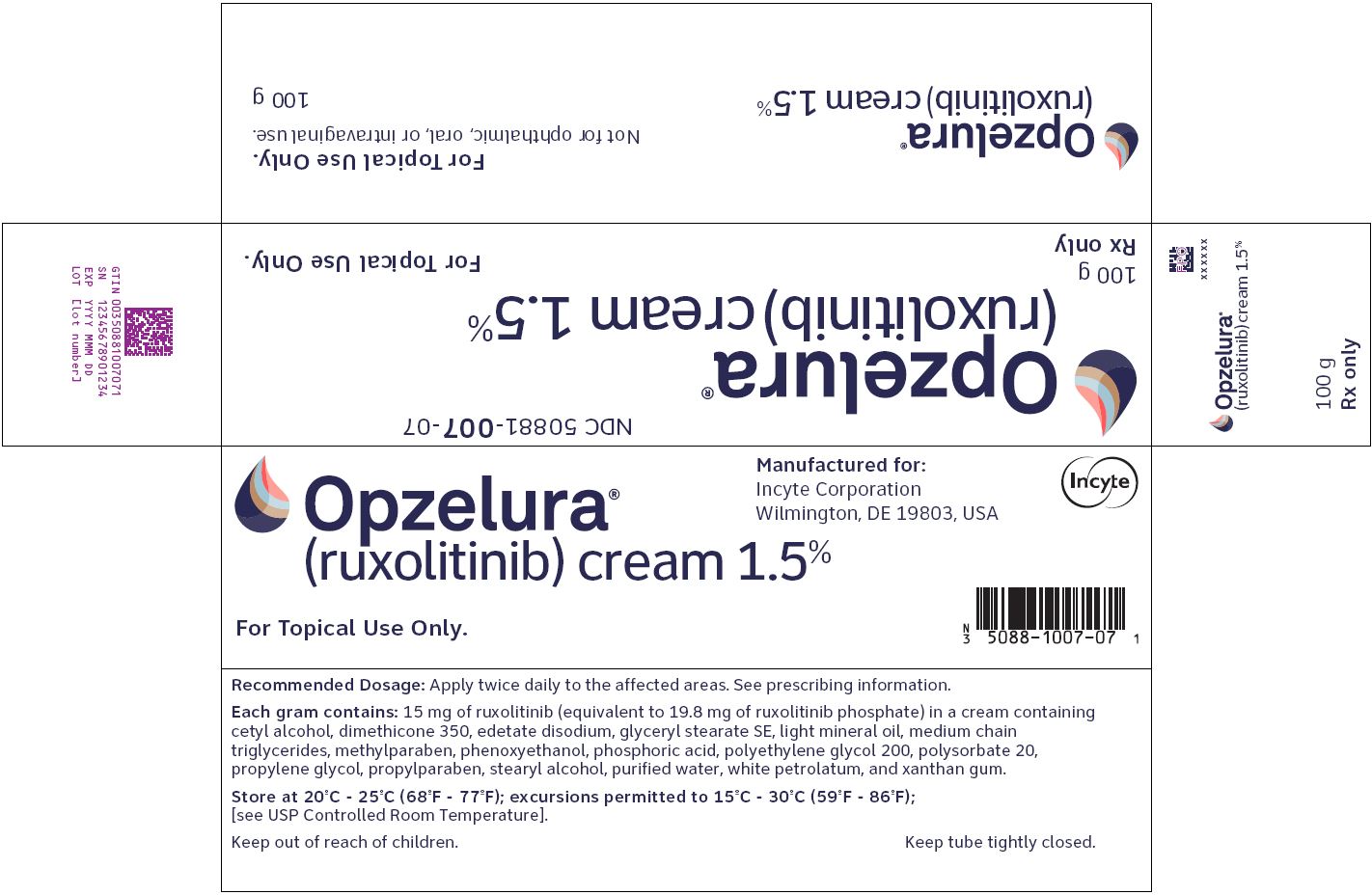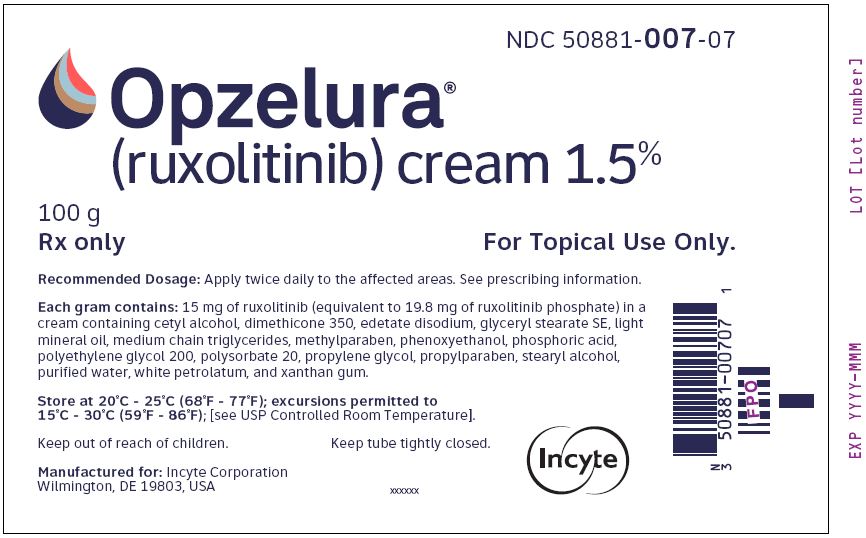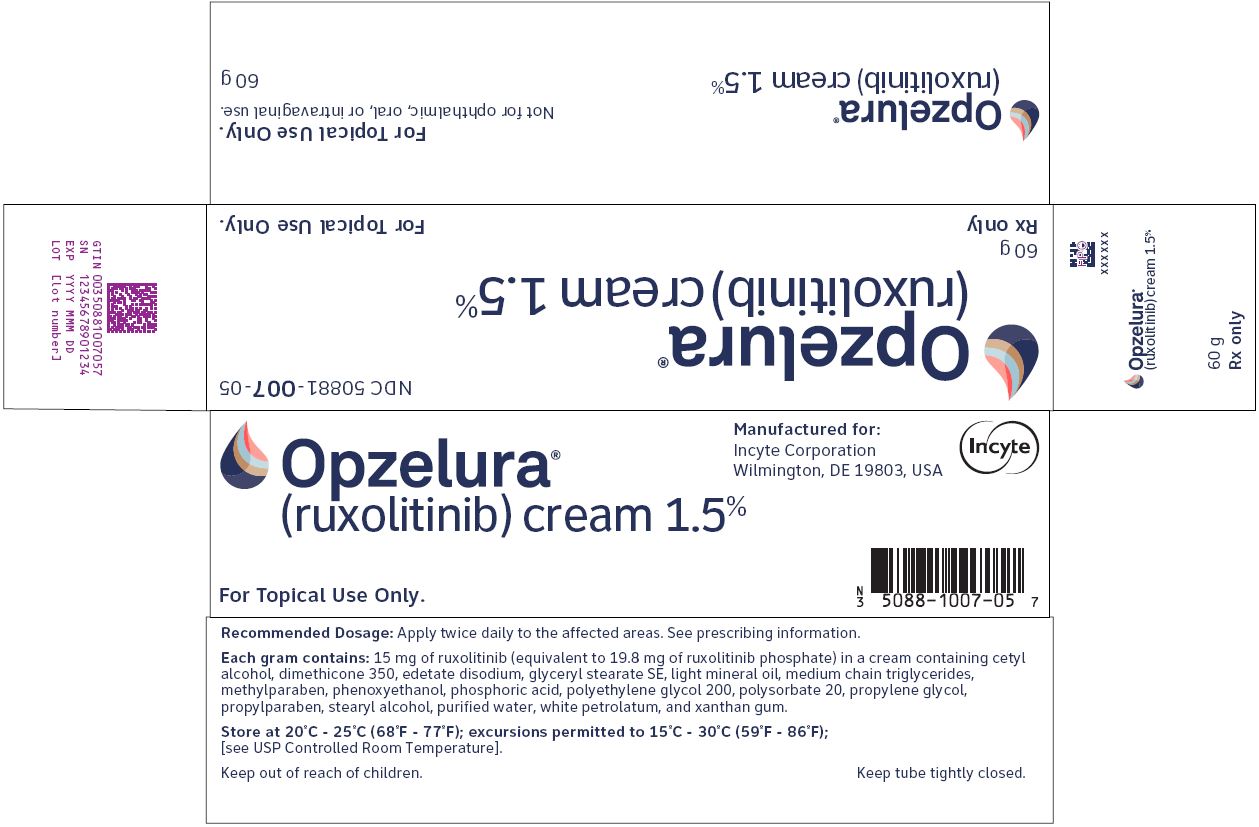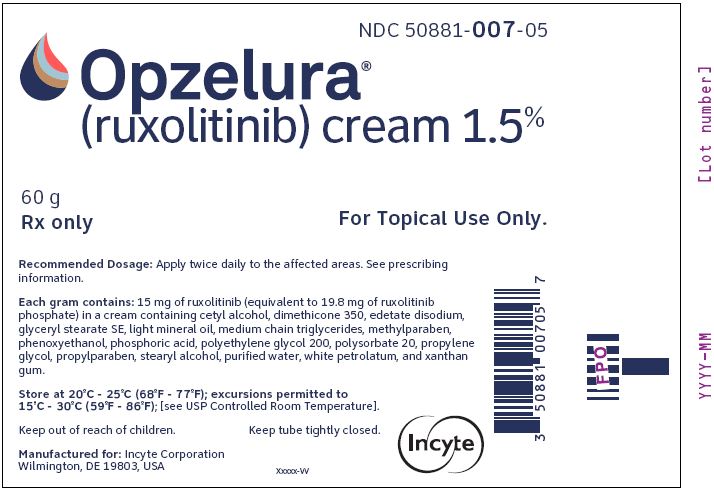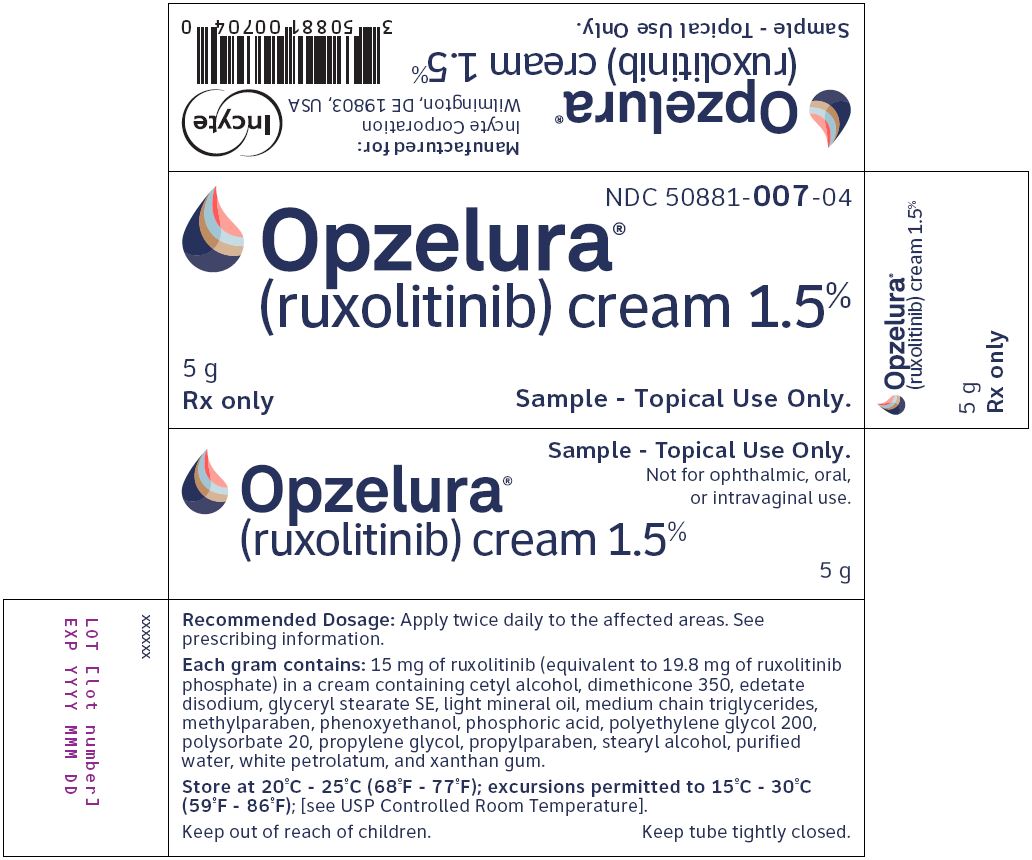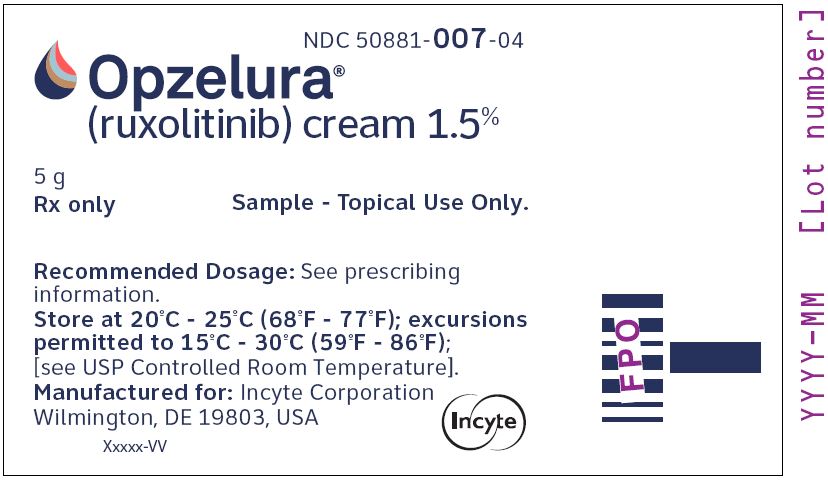 DRUG LABEL: OPZELURA
NDC: 50881-007 | Form: CREAM
Manufacturer: Incyte Corporation
Category: prescription | Type: HUMAN PRESCRIPTION DRUG LABEL
Date: 20251111

ACTIVE INGREDIENTS: RUXOLITINIB PHOSPHATE 15 mg/1 g
INACTIVE INGREDIENTS: CETYL ALCOHOL; DIMETHICONE 350; EDETATE DISODIUM; GLYCERYL STEARATE SE; LIGHT MINERAL OIL; MEDIUM-CHAIN TRIGLYCERIDES; METHYLPARABEN; PHENOXYETHANOL; PHOSPHORIC ACID; POLYETHYLENE GLYCOL 200; POLYSORBATE 20; PROPYLENE GLYCOL; PROPYLPARABEN; STEARYL ALCOHOL; WATER; WHITE PETROLATUM; XANTHAN GUM

HIGHLIGHTS OF PRESCRIBING INFORMATION

These highlights do not include all the information needed to use OPZELURA cream safely and effectively. See full prescribing information for OPZELURA cream.
OPZELURA® (ruxolitinib) cream, for topical use
Initial U.S. Approval: 2011

WARNING: SERIOUS INFECTIONS, MORTALITY, MALIGNANCY, MAJOR ADVERSE CARDIOVASCULAR EVENTS, AND THROMBOSIS

WARNING: SERIOUS INFECTIONS, MORTALITY, MALIGNANCY, MAJOR ADVERSE CARDIOVASCULAR EVENTS (MACE), AND THROMBOSIS

See full prescribing information for complete boxed warning.

- Serious infections leading to hospitalization or death, including tuberculosis and bacterial, invasive fungal, viral, and other opportunistic infections, have occurred in patients receiving Janus kinase inhibitors for inflammatory conditions. (5.1)
- Higher rate of all-cause mortality, including sudden cardiovascular death have been observed in patients treated with Janus kinase inhibitors for inflammatory conditions. (5.2)
- Lymphoma and other malignancies have been observed in patients treated with Janus kinase inhibitors for inflammatory conditions. (5.3)
- Higher rate of MACE (including cardiovascular death, myocardial infarction, and stroke) has been observed in patients treated with Janus kinase inhibitors for inflammatory conditions. (5.4)
- Thrombosis, including deep venous thrombosis, pulmonary embolism, and arterial thrombosis, some fatal, have occurred in patients treated with Janus kinase inhibitors for inflammatory conditions. (5.5)

RECENT MAJOR CHANGES

Indications and Usage (1.1) | 09/2025
Dosage and Administration (2.1) | 09/2025
Warnings and Precautions (5.6) | 09/2025

1 INDICATIONS AND USAGE

OPZELURA is a Janus kinase (JAK) inhibitor indicated for:

- the topical short-term and non-continuous chronic treatment of mild to moderate atopic dermatitis in non-immunocompromised adult and pediatric patients 2 years of age and older whose disease is not adequately controlled with topical prescription therapies or when those therapies are not advisable. (1.1)
- the topical treatment of nonsegmental vitiligo in adult and pediatric patients 12 years of age and older. (1.2)

Limitations of Use

Use of OPZELURA in combination with therapeutic biologics, other JAK inhibitors or potent immunosuppressants such as azathioprine or cyclosporine is not recommended. (1.3)

2 DOSAGE AND ADMINISTRATION

Atopic Dermatitis

- Apply a thin layer of OPZELURA topically twice daily to affected areas of up to 20% body surface area. (2.1)
- Do not use OPZELURA with occlusive dressings. (2.1)

Adult and Pediatric Patients 12 Years of Age and Older

- Do not use more than one 60 gram tube of OPZELURA per week or one 100 gram tube per 2 weeks. (2.1)

Pediatric Patients 2 to 11 Years of Age

- Do not use more than one 60 gram tube of OPZELURA per 2 weeks. (2.1)

Nonsegmental Vitiligo

- Apply a thin layer of OPZELURA topically twice daily to affected areas of up to 10% body surface area. (2.2)

- Do not use more than one 60 gram tube of OPZELURA per week or one 100 gram tube per 2 weeks. (2.2)

3 DOSAGE FORMS AND STRENGTHS

Cream: 1.5% ruxolitinib supplied in 60 g and 100 g tubes (3)

4 CONTRAINDICATIONS

None. (4)

5 WARNINGS AND PRECAUTIONS

- Serious Infections: Serious bacterial, mycobacterial, fungal and viral infections have occurred. Regularly monitor patients for infection and manage it promptly. (5.1)
- Non-melanoma Skin Cancers. Basal cell and squamous cell carcinoma have occurred. Perform periodic skin examinations during treatment and following treatment as appropriate. (5.3)
- Thrombosis. Thromboembolic events have occurred. (5.5)
- Cytopenias: Thrombocytopenia, anemia, neutropenia, lymphopenia, and leukopenia have occurred. Perform CBC monitoring as clinically indicated. (5.6)

6 ADVERSE REACTIONS

- In atopic dermatitis, the most common adverse reactions (incidence ≥ 1%) are nasopharyngitis, diarrhea, bronchitis, ear infection, eosinophil count increased, urticaria, folliculitis, tonsillitis, rhinorrhea, upper respiratory tract infection, COVID-19, application site reactions, pyrexia, and white blood cell decreased. (6)
- In nonsegmental vitiligo, the most common adverse reactions (incidence ≥ 1%) are application site acne, application site pruritus, nasopharyngitis, headache, urinary tract infection, application site erythema, and pyrexia. (6)

To report SUSPECTED ADVERSE REACTIONS, contact Incyte Corporation at 1-855-463-3463 or FDA at 1-800-FDA-1088 or www.fda.gov/medwatch.

8 USE IN SPECIFIC POPULATIONS

- Lactation: Advise not to breastfeed. (8.2)

FULL PRESCRIBING INFORMATION

WARNING: SERIOUS INFECTIONS, MORTALITY, MALIGNANCY, MAJOR ADVERSE CARDIOVASCULAR EVENTS, AND THROMBOSIS

SERIOUS INFECTIONS
Patients treated with oral Janus kinase inhibitors for inflammatory conditions are at risk for developing serious infections that may lead to hospitalization or death [see Warnings and Precautions (5.1) and Adverse Reactions (6.1)].

Reported infections include:

- Active tuberculosis, which may present with pulmonary or extrapulmonary disease.
- Invasive fungal infections, including cryptococcosis, and pneumocystosis.
- Bacterial, viral, including herpes zoster, and other infections due to opportunistic pathogens.

Avoid use of OPZELURA in patients with an active, serious infection, including localized infections. If a serious infection develops, interrupt OPZELURA until the infection is controlled.

The risks and benefits of treatment with OPZELURA should be carefully considered prior to initiating therapy in patients with chronic or recurrent infection.

Patients should be closely monitored for the development of signs and symptoms of infection during and after treatment with OPZELURA [see Warnings and Precautions (5.1)].

MORTALITY

In a large, randomized, postmarketing safety study in rheumatoid arthritis (RA) patients 50 years of age and older with at least one cardiovascular risk factor comparing an oral JAK inhibitor to tumor necrosis factor (TNF) blocker treatment, a higher rate of all-cause mortality, including sudden cardiovascular death, was observed with the JAK inhibitor [see Warnings and Precautions (5.2)].

MALIGNANCIES

Malignancies were reported in patients treated with OPZELURA. Lymphoma and other malignancies have been observed in patients receiving JAK inhibitors used to treat inflammatory conditions. In RA patients treated with an oral JAK inhibitor, a higher rate of malignancies (excluding non-melanoma skin cancer (NMSC)) was observed when compared with TNF blockers. Patients who are current or past smokers are at additional increased risk [see Warnings and Precautions (5.3)].

MAJOR ADVERSE CARDIOVASCULAR EVENTS (MACE)

In RA patients 50 years of age and older with at least one cardiovascular risk factor treated with an oral JAK inhibitor, a higher rate of major adverse cardiovascular events (MACE) (defined as cardiovascular death, myocardial infarction, and stroke), was observed when compared with TNF blockers. Patients who are current or past smokers are at additional increased risk. Discontinue OPZELURA in patients who have experienced a myocardial infarction or stroke [see Warnings and Precautions (5.4)].

THROMBOSIS

Thromboembolic events were observed in trials with OPZELURA. Thrombosis, including pulmonary embolism (PE), deep venous thrombosis (DVT), and arterial thrombosis have been reported in patients receiving JAK inhibitors used to treat inflammatory conditions. Many of these adverse reactions were serious and some resulted in death. In RA patients 50 years of age and older with at least one cardiovascular risk factor treated with an oral JAK inhibitor, a higher rate of thrombosis was observed when compared with TNF blockers. Avoid OPZELURA in patients at risk. If symptoms of thrombosis occur, discontinue OPZELURA and treat appropriately [see Warnings and Precautions (5.5)].

RECENT MAJOR CHANGES

Boxed Warning7/2022

Indications and Usage (1.2, 1.3)7/2022

Dosage and Administration (2.1, 2.3)7/2022

Warnings and Precautions (5.2, 5.3, 5.4, 5.5)7/2022

1 INDICATIONS AND USAGE

1.1 Atopic Dermatitis

OPZELURA is indicated for the topical short-term and non-continuous chronic treatment of mild to moderate atopic dermatitis in non-immunocompromised adult and pediatric patients 2 years of age and older whose disease is not adequately controlled with topical prescription therapies or when those therapies are not advisable.

1.2 Nonsegmental Vitiligo

OPZELURA is indicated for the topical treatment of nonsegmental vitiligo in adult and pediatric patients 12 years of age and older.

1.3 Limitations of Use

Use of OPZELURA in combination with therapeutic biologics, other Janus kinase (JAK) inhibitors, or potent immunosuppressants such as azathioprine or cyclosporine is not recommended.

2 DOSAGE AND ADMINISTRATION

2.1 Recommended Dosage and Administration for Atopic Dermatitis

OPZELURA is for topical use only. OPZELURA is not for ophthalmic, oral, or intravaginal use.

Instruct patients to apply a thin layer of OPZELURA twice daily to affected areas of up to 20% body surface area.

Do not use OPZELURA with occlusive dressings.

Stop using when signs and symptoms (e.g., itch, rash, and redness) of atopic dermatitis resolve. If signs and symptoms do not improve within 8 weeks, patients should be re-examined by their healthcare provider [see Clinical Studies (14.1)].

Adult and Pediatric Patients 12 Years of Age and Older

Do not use more than one 60 gram tube of OPZELURA per week or one 100 gram tube per 2 weeks.

Pediatric Patients 2 to 11 Years of Age

Do not use more than one 60 gram tube of OPZELURA per 2 weeks.

2.2 Recommended Dosage and Administration for Nonsegmental Vitiligo

OPZELURA is for topical use only. OPZELURA is not for ophthalmic, oral, or intravaginal use.

Instruct patients to apply a thin layer of OPZELURA twice daily to affected areas of up to 10% body surface area.

Do not use more than one 60 gram tube of OPZELURA per week or one 100 gram tube per 2 weeks.

Satisfactory patient response may require treatment with OPZELURA for more than 24 weeks. If the patient does not find the repigmentation meaningful by 24 weeks, the patient should be re‑evaluated by the healthcare provider [see Clinical Studies (14.2)].

3 DOSAGE FORMS AND STRENGTHS

Cream: 15 mg of ruxolitinib per gram (1.5%) of white to off-white cream supplied in 60 g and 100 g tubes

4 CONTRAINDICATIONS

None.

5 WARNINGS AND PRECAUTIONS

5.1 Serious Infections

Serious and sometimes fatal infections due to bacterial, mycobacterial, invasive fungal, viral, or other opportunistic pathogens have been reported in patients receiving oral JAK inhibitors.

Serious lower respiratory tract infections were reported in the clinical development program with topical ruxolitinib.

Avoid use of OPZELURA in patients with an active, serious infection, including localized infections. Consider the risks and benefits of treatment prior to initiating OPZELURA in patients:

- with chronic or recurrent infection
- with a history of a serious or an opportunistic infection
- who have been exposed to tuberculosis
- who have resided or traveled in areas of endemic tuberculosis or endemic mycoses; or
- with underlying conditions that may predispose them to infection.

Closely monitor patients for the development of signs and symptoms of infection during and after treatment with OPZELURA. Interrupt OPZELURA if a patient develops a serious infection, an opportunistic infection, or sepsis. Do not resume OPZELURA until the infection is controlled.

Tuberculosis

No cases of active tuberculosis (TB) were reported in clinical trials with OPZELURA. Cases of active TB were reported in clinical trials of oral JAK inhibitors used to treat inflammatory conditions. Consider evaluating patients for latent and active TB infection prior to administration of OPZELURA.

During OPZELURA use, monitor patients for the development of signs and symptoms of TB.

Viral Reactivation

Viral reactivation, including cases of herpes virus reactivation (e.g., herpes zoster), were reported in clinical trials with JAK inhibitors used to treat inflammatory conditions including OPZELURA. If a patient develops herpes zoster, consider interrupting OPZELURA treatment until the episode resolves.

Hepatitis B and C

The impact of JAK inhibitors used to treat inflammatory conditions including OPZELURA on chronic viral hepatitis reactivation is unknown. Patients with a history of hepatitis B or C infection were excluded from clinical trials.

Hepatitis B viral load (HBV-DNA titer) increases, with or without associated elevations in alanine aminotransferase and aspartate aminotransferase, have been reported in patients with chronic HBV infections taking oral ruxolitinib.

OPZELURA initiation is not recommended in patients with active hepatitis B or hepatitis C.

5.2 Mortality

In a large, randomized, postmarketing safety study of an oral JAK inhibitor in rheumatoid arthritis (RA) patients 50 years of age and older with at least one cardiovascular risk factor, a higher rate of all-cause mortality, including sudden cardiovascular death, was observed in patients treated with the JAK inhibitor compared with TNF blockers.

Consider the benefits and risks for the individual patient prior to initiating or continuing therapy with OPZELURA.

5.3 Malignancy and Lymphoproliferative Disorders

Malignancies, including lymphomas, were observed in clinical trials of oral JAK inhibitors used to treat inflammatory conditions. Patients who are current or past smokers are at additional increased risk.

Malignancies, including lymphomas, have occurred in patients receiving JAK inhibitors used to treat inflammatory conditions. In a large, randomized, postmarketing safety study of an oral JAK inhibitor in RA patients, a higher rate of malignancies (excluding non-melanoma skin cancer) was observed in patients treated with the JAK inhibitor compared to those treated with TNF blockers. A higher rate of lymphomas was observed in patients treated with the JAK inhibitor compared to those treated with TNF blockers. A higher rate of lung cancers was observed in current or past smokers treated with the JAK inhibitor compared to those treated with TNF blockers. In this study, current or past smokers had an additional increased risk of overall malignancies.

Consider the benefits and risks for the individual patient prior to initiating or continuing therapy with OPZELURA, particularly in patients with a known malignancy (other than successfully treated non-melanoma skin cancers), patients who develop a malignancy when on treatment, and patients who are current or past smokers.

Non-melanoma Skin Cancers

Non-melanoma skin cancers including basal cell and squamous cell carcinoma have occurred in patients treated with OPZELURA. Perform periodic skin examinations during OPZELURA treatment and following treatment as appropriate. Exposure to sunlight and UV light should be limited by wearing protective clothing and using broad-spectrum sunscreen.

5.4 Major Adverse Cardiovascular Events (MACE)

In a large, randomized, postmarketing safety study of an oral JAK inhibitor in RA patients 50 years of age and older with at least one cardiovascular risk factor, a higher rate of major adverse cardiovascular events (MACE) defined as cardiovascular death, non-fatal myocardial infarction (MI), and non-fatal stroke was observed with the JAK inhibitor compared to those treated with TNF blockers. Patients who are current or past smokers are at additional increased risk.

Consider the benefits and risks for the individual patient prior to initiating or continuing therapy with OPZELURA, particularly in patients who are current or past smokers and patients with other cardiovascular risk factors. Patients should be informed about the symptoms of serious cardiovascular events and the steps to take if they occur. Discontinue OPZELURA in patients that have experienced a myocardial infarction or stroke.

5.5 Thrombosis

Thromboembolic events were observed in clinical trials with OPZELURA.

Thrombosis, including deep vein thrombosis (DVT), pulmonary embolism (PE), and arterial thrombosis have been reported in patients receiving JAK inhibitors used to treat inflammatory conditions. Many of these adverse reactions were serious and some resulted in death.

In a large, randomized, postmarketing safety study of an oral JAK inhibitor in RA patients 50 years of age and older with at least one cardiovascular risk factor, higher rates of overall thrombosis, DVT, and PE were observed compared to those treated with TNF blockers.

Avoid OPZELURA in patients who may be at increased risk of thrombosis. If symptoms of thrombosis occur, discontinue OPZELURA and evaluate and treat patients appropriately.

5.6 Cytopenias

Thrombocytopenia, anemia, neutropenia, lymphopenia, and leukopenia were reported in the clinical trials with OPZELURA. Consider the benefits and risks for individual patients who have a known history of these events prior to initiating therapy with OPZELURA. Perform CBC monitoring as clinically indicated. Discontinue OPZELURA if signs and/or symptoms associated with clinically significant decreases in laboratory values occur.

5.7 Lipid Elevations

Treatment with oral ruxolitinib has been associated with increases in lipid parameters including total cholesterol, low-density lipoprotein (LDL) cholesterol, and triglycerides.

6 ADVERSE REACTIONS

6.1 Clinical Trials Experience

Because clinical trials are conducted under widely varying conditions, adverse reaction rates observed in the clinical trials of a drug cannot be directly compared to rates in the clinical trials of another drug and may not reflect the rates observed in practice.

Adverse Reactions in Adult and Pediatric Subjects 2 Years of Age and Older with Atopic Dermatitis

Adult and Pediatric Subjects 12 Years of Age and Older

In two double-blind, vehicle-controlled clinical trials (TRuE-AD1 and TRuE-AD2), 499 adult and pediatric subjects 12 years of age and older with atopic dermatitis were treated topically with OPZELURA twice daily for 8 weeks [see Clinical Studies (14.1)]. The adverse reactions reported by ≥ 1% of OPZELURA treated subjects and at a greater incidence than in the vehicle arm are listed in Table 1.

Table 1: Adverse Reactions Occurring in ≥ 1% of Adult and Pediatric Subjects 12 Years of Age and Older Treated with OPZELURA for Atopic Dermatitis through Week 8 in TRuE-AD1 and TRuE-AD2
Adverse Reaction | OPZELURA (N = 499) n (%) | Vehicle (N = 250) n (%)
Nasopharyngitis | 13 (3) | 2 (1)
Bronchitis | 4 (1) | 0 (0)
Ear infection | 4 (1) | 0 (0)
Eosinophil count increased | 4 (1) | 0 (0)
Urticaria | 4 (1) | 0 (0)
Diarrhea | 3 (1) | 1 (< 1)
Folliculitis | 3 (1) | 0 (0)
Tonsillitis | 3 (1) | 0 (0)
Rhinorrhea | 3 (1) | 1 (< 1)

Adverse reactions that occurred in TRuE-AD1 and TRuE-AD2 in < 1% of subjects in the OPZELURA group and none in the vehicle group were: neutropenia, allergic conjunctivitis, pyrexia, seasonal allergy, herpes zoster, otitis externa, Staphylococcal infection, and acneiform dermatitis.

No clinically meaningful differences in safety or effectiveness were observed between adult and pediatric subjects 12 to 17 years of age.

Pediatric Subjects 2 to 11 Years of Age

In a double-blind, vehicle-controlled clinical trial (TRuE-AD3), 130 pediatric subjects 2 to 11 years of age with mild to moderate atopic dermatitis were treated topically with OPZELURA twice daily for 8 weeks [see Clinical Studies (14.1)]. The adverse reactions reported by ≥ 1% of subjects treated with OPZELURA and at a greater incidence than in the vehicle arm are listed in Table 2.

Table 2: Adverse Reactions Occurring in ≥ 1% Pediatric Subjects 2 to 11 Years of Age Treated with OPZELURA for Atopic Dermatitis through Week 8 in TRuE-AD3
Adverse Reaction | OPZELURA (N = 130) n (%) | Vehicle (N = 65) n (%)
Upper respiratory tract infection [Upper respiratory tract infection includes upper respiratory tract infection, nasopharyngitis, rhinorrhea, oropharyngeal pain, respiratory tract congestion, viral upper respiratory tract infection] | 20 (15) | 7 (11)
COVID-19 | 6 (5) | 2 (3)
Application site reaction [Application site reaction includes application site pain, application site irritation, application site discomfort, application site pruritus] | 6 (5) | 1 (2)
Pyrexia | 3 (2) | 0 (0)
White blood cell decreased [White blood cell decreased includes white blood cell decreased, leukopenia] | 2 (2) | 0 (0)

Subjects with cytopenias (defined as hemoglobin < 10 g/dL, absolute neutrophil count (ANC) < 1000/μL, and platelet count < 100,000/μL) at screening were excluded from the trial. The impact of OPZELURA on blood cell counts in this population has not been studied.

Adverse Reactions in Adult and Pediatric Subjects 12 Years of Age and Older with Nonsegmental Vitiligo

In two double-blind, vehicle-controlled clinical trials (TRuE-V1 and TRuE-V2), 449 adult and pediatric subjects 12 years of age and older with nonsegmental vitiligo were treated topically with OPZELURA twice daily for 24 weeks [see Clinical Studies (14.2)]. The adverse reactions reported by OPZELURA treated subjects with an incidence of ≥ 1% and at least 1% greater incidence than in the vehicle arm in the 24-week double-blind period are listed in Table 3.

Table 3: Adverse Reactions Occurring in ≥ 1% of Adult and Pediatric Subjects 12 Years of Age and Older Treated with OPZELURA for Nonsegmental Vitiligo through Week 24 in TRuE-V1 and TRuE-V2
Adverse Reaction | OPZELURA (N = 449) n (%) | Vehicle (N = 224) n (%)
Application site acne | 26 (6) | 2 (1)
Application site pruritus | 23 (5) | 6 (3)
Nasopharyngitis | 19 (4) | 5 (2)
Headache | 17 (4) | 6 (3)
Urinary tract infection | 7 (2) | 1 (< 1)
Application site erythema | 7 (2) | 1 (< 1)
Pyrexia | 6 (1) | 0

Adverse reactions that occurred in TRuE-V1 and TRuE-V2 in ≥ 0.5% to < 1% of subjects in the OPZELURA group and none in the vehicle group were: application site dermatitis, hypertension, anxiety, application site discoloration, application site folliculitis, dermatitis contact, diarrhea, ear infection, gastritis, gastroenteritis, hordeolum, influenza-like illness, insomnia, nasal congestion, and vomiting.

No clinically meaningful differences in safety or effectiveness were observed between adults and pediatric subjects.

7 DRUG INTERACTIONS

Drug interaction studies with OPZELURA have not been conducted.

Ruxolitinib is known to be a substrate for cytochrome P450 3A4 (CYP3A4). Inhibitors of CYP3A4 may increase ruxolitinib systemic concentrations whereas inducers of CYP3A4 may decrease ruxolitinib systemic concentrations [see Clinical Pharmacology (12.3)].

Strong Inhibitors of CYP3A4

Avoid concomitant use of OPZELURA with strong inhibitors of CYP3A4 as there is a potential to increase the systemic exposure of ruxolitinib and could increase the risk of OPZELURA adverse reactions [see Clinical Pharmacology (12.3)].

8 USE IN SPECIFIC POPULATIONS

8.1 Pregnancy

Pregnancy Exposure Registry

There is a pregnancy registry that monitors pregnancy outcomes in pregnant persons exposed to OPZELURA during pregnancy. Pregnant persons exposed to OPZELURA and healthcare providers should report OPZELURA exposure by calling 1-855-463-3463 or visiting www.opzelura.pregnancy.incyte.com.

Risk Summary

Available data from pregnancies reported in clinical trials with OPZELURA are not sufficient to evaluate a drug-associated risk for major birth defects, miscarriage, or other adverse maternal or fetal outcomes. In animal reproduction studies, oral administration of ruxolitinib to pregnant rats and rabbits during the period of organogenesis resulted in adverse developmental outcomes at doses associated with maternal toxicity (see Data).

The background risks of major birth defects and miscarriage for the indicated populations are unknown. All pregnancies carry some risk of birth defects, loss, or other adverse outcomes. The background risk in the U.S. general population of major birth defects and miscarriage is 2-4% and 15-20%, respectively.

Data

Animal Data

Ruxolitinib was administered orally to pregnant rats or rabbits during the period of organogenesis, at doses of 15, 30, or 60 mg/kg/day in rats and 10, 30, or 60 mg/kg/day in rabbits. There were no treatment-related malformations at any dose. A decrease in fetal weight of approximately 9% was noted in rats at the highest and maternally toxic dose of 60 mg/kg/day. This dose resulted in systemic exposure approximately 22 times the clinical systemic exposure at the maximum recommended human dose (MRHD; the clinical systemic exposure from ruxolitinib cream, 1.5% applied twice daily to 25-40% atopic dermatitis-affected body surface area is used for calculation of multiples of human exposure). In rabbits, lower fetal weights of approximately 8% and increased late resorptions were noted at the highest and maternally toxic dose of 60 mg/kg/day. This dose resulted in systemic exposure approximately 70% the MRHD clinical systemic exposure.

In a pre-and post-natal development study in rats, pregnant animals were dosed with ruxolitinib from implantation through lactation at doses up to 30 mg/kg/day. There were no drug-related adverse effects on embryofetal survival, postnatal growth, development parameters or offspring reproductive function at the highest dose evaluated (3.1 times the MRHD clinical systemic exposure).

8.2 Lactation

Risk Summary

There are no data on the presence of ruxolitinib in human milk, the effects on the breastfed child, or the effects on milk production. Ruxolitinib was present in the milk of lactating rats (see Data). When a drug is present in animal milk, it is likely that the drug will be present in human milk. Because of the serious adverse findings in adults, including risks of serious infections, thrombocytopenia, anemia, and neutropenia, advise women not to breastfeed during treatment with OPZELURA and for approximately four weeks after the last dose (approximately 5‑6 elimination half-lives).

Data

Lactating rats were administered a single dose of [14C]-labeled ruxolitinib (30 mg/kg) on postnatal Day 10, after which plasma and milk samples were collected for up to 24 hours. The AUC for total radioactivity in milk was approximately 13 times the maternal plasma AUC. Additional analysis showed the presence of ruxolitinib and several of its metabolites in milk, all at levels higher than those in maternal plasma.

8.4 Pediatric Use

Atopic Dermatitis

The safety and effectiveness of OPZELURA for the topical short-term and non-continuous chronic treatment of mild to moderate atopic dermatitis have been established in non-immunocompromised pediatric patients ages 2 years and older whose disease is not adequately controlled with topical prescription therapies or when those therapies are not advisable. Use of OPZELURA in this age group is supported by evidence from adequate and well-controlled trials in adults and pediatric subjects ages 2 years and older with mild to moderate atopic dermatitis [see Clinical Studies (14.1)]. Trials included 92 subjects 12 to 17 years of age and 130 subjects 2 to 11 years of age treated with OPZELURA.

Application site reactions, pyrexia, and decreased white blood cell were reported more frequently in pediatric subjects ages 2 to ll years compared to adults and pediatric subjects ages 12 years and older [see Adverse Reactions (6.1)]. The safety and effectiveness of OPZELURA have not been established in pediatric patients younger than 2 years of age with atopic dermatitis.

Nonsegmental Vitiligo

The safety and effectiveness of OPZELURA for the topical treatment of nonsegmental vitiligo have been established in pediatric patients ages 12 years and older. Use of OPZELURA in this age group is supported by evidence from TRuE-V1 and TRuE-V2, which included 55 subjects ages 12 to 17 years with nonsegmental vitiligo [see Clinical Studies (14.2)].

The safety and effectiveness of OPZELURA have not been established in pediatric patients younger than 12 years of age with nonsegmental vitiligo.

Juvenile Animal Toxicity Data

Oral administration of ruxolitinib to juvenile rats resulted in effects on growth and bone measures. When administered starting at postnatal day 7 (the equivalent of a human newborn) at doses of 1.5 to 75 mg/kg/day, evidence of fractures occurred at doses ≥ 30 mg/kg/day, and effects on body weight and other bone measures [e.g., bone mineral content, peripheral quantitative computed tomography, and x-ray analysis] occurred at doses ≥ 5 mg/kg/day. When administered starting at postnatal day 21 (the equivalent of a human 2-3 years of age) at doses of 5 to 60 mg/kg/day, effects on body weight and bone occurred at doses ≥ 15 mg/kg/day, which were considered adverse at 60 mg/kg/day. Males were more severely affected than females in all age groups, and effects were generally more severe when administration was initiated earlier in the postnatal period. These findings were observed at systemic exposures that are at least 45% the MRHD in pediatric subjects 2 to 11 years of age (the clinical systemic exposure from ruxolitinib cream, 1.5% applied twice daily to 35-50% atopic dermatitis-affected body surface area in pediatric subjects 2 to 11 years of age is used for the calculation of multiples of human exposure in this subsection).

8.5 Geriatric Use

Of the 1249 total subjects with atopic dermatitis in clinical trials with OPZELURA, 115 (9%) were 65 years of age and older [see Clinical Studies (14.1)]. No clinically meaningful differences in safety or effectiveness were observed between subjects less than 65 years and subjects 65 years and older.

Of the 831 total subjects enrolled with nonsegmental vitiligo in clinical trials with OPZELURA, 65 (8%) were 65 years of age and older [see Clinical Studies (14.2)]. Clinical trials of OPZELURA in subjects with nonsegmental vitiligo did not include sufficient numbers of subjects 65 years of age and older to determine whether they respond differently from younger adult subjects.

11 DESCRIPTION

Ruxolitinib phosphate is a Janus kinase inhibitor with the chemical name (R)-3-(4-(7H-pyrrolo[2,3-d]pyrimidin-4-yl)-1H-pyrazol-1-yl)-3-cyclopentylpropanenitrile phosphate and a molecular weight of 404.36 g/mol. Ruxolitinib phosphate has the following structural formula:
Ruxolitinib phosphate is a white to off-white to light yellow to light pink powder.
OPZELURA (ruxolitinib) cream is a white to off-white oil-in-water, solubilized emulsion cream for topical use.
Each gram of OPZELURA contains 15 mg of ruxolitinib (equivalent to 19.8 mg of ruxolitinib phosphate) in a cream containing cetyl alcohol, dimethicone 350, edetate disodium, glyceryl stearate SE, light mineral oil, medium chain triglycerides, methylparaben, phenoxyethanol, phosphoric acid, polyethylene glycol 200, polysorbate 20, propylene glycol, propylparaben, stearyl alcohol, purified water, white petrolatum, and xanthan gum.

12 CLINICAL PHARMACOLOGY

12.1 Mechanism of Action

Ruxolitinib, a Janus kinase (JAK) inhibitor, inhibits JAK1 and JAK2 which mediate the signaling of a number of cytokines and growth factors that are important for hematopoiesis and immune function. JAK signaling involves recruitment of STATs (signal transducers and activators of transcription) to cytokine receptors, activation and subsequent localization of STATs to the nucleus leading to modulation of gene expression. The relevance of inhibition of specific JAK enzymes to therapeutic effectiveness is not currently known.

12.2 Pharmacodynamics

The pharmacodynamics of OPZELURA is unknown.

Cardiac Electrophysiology

Under the conditions of clinical use, OPZELURA is not expected to prolong the QT interval.

12.3 Pharmacokinetics

In Trial INCB18424-103, the pharmacokinetics of ruxolitinib were evaluated in 20 adult subjects and 21 pediatric subjects 13 years of age and older with atopic dermatitis with a mean ± SD BSA involvement of 37.5 ± 16.1% (range 25% to 90%). Subjects applied approximately 1.5 mg/cm^2 of OPZELURA (dose range was approximately 1.2 grams to 37.6 grams per application) twice daily for 28 days.

Absorption

Plasma concentrations of ruxolitinib were quantifiable in all subjects. In adult subjects, the mean ± SD maximum plasma concentration (Cmax) and area under the concentration time curve from 0 to 12 hours post dose (AUC0–12) for ruxolitinib on Day 1 were 449 ± 883 nM and 3215 ± 6184 h*nM, respectively.

There is no evidence of ruxolitinib accumulation after daily application of OPZELURA for 28 days in subjects with atopic dermatitis.

Distribution

Plasma protein binding is approximately 97%.

Elimination

The mean terminal half-life of ruxolitinib following topical application of OPZELURA was estimated in 9 subjects and is approximately 116 hours.

Metabolism

Ruxolitinib is primarily metabolized by CYP3A4 and to a lesser extent by CYP2C9 in vitro.

Excretion

Ruxolitinib and its metabolites are primarily excreted by urine (74%) and feces (22%). Less than 1% is excreted as unchanged drug.

Specific Populations

Pediatric Patients

In Trial INCB18424-103, in subjects 13 to 17 years of age with atopic dermatitis, the mean ± SD Cmax and AUC0–12 for ruxolitinib on Day 1 were 110 ± 255 nM and 801 ± 2019 h*nM, respectively.

In Trial INCB18424-109, the pharmacokinetics of ruxolitinib was evaluated in 27 subjects 2 to 11 years of age with atopic dermatitis with a mean ± SD BSA involvement of 58.9 ± 20.6% (range 35% to 92%). The mean ± SD daily dose of the cream was 8.5 ± 6.3 g. Plasma concentrations of ruxolitinib were quantifiable in all subjects. The mean ± SD steady state plasma concentration (Css) and projected area under the concentration time curve from 0 to 12 hours post dose (AUC0-12h) for ruxolitinib were 84.1 ± 183 nM and 1009.2 ± 2196 h*nM, respectively in subjects 7 to less than 12 years of age (n=12) and 109 ± 122 nM and 1308 ± 1464 h*nM, respectively in subjects 2 to less than 7 years of age (n=15).

There is no evidence of ruxolitinib accumulation after twice daily application of OPZELURA for 28 days in subjects 2 years to 17 years of age with atopic dermatitis.

Drug Interactions

Clinical Studies

Drug interaction studies with OPZELURA have not been conducted.

- Strong CYP3A4 inhibitors: The Cmax and AUC of ruxolitinib increased 33% and 91%, respectively, with administration of 10 mg single dose orally following ketoconazole 200 mg twice daily for four days, compared to receiving the oral ruxolitinib dose alone in healthy subjects.
- Mild or moderate CYP3A4 inhibitors: There was an 8% and 27% increase in the Cmax and AUC of ruxolitinib, respectively, with the administration of 10 mg single dose orally following erythromycin, a moderate CYP3A4 inhibitor, at 500 mg twice daily for 4 days, compared to receiving the oral ruxolitinib dose alone in healthy subjects. There are no clinical studies conducted with mild CYP3A4 inhibitor.
- CYP3A4 inducers: The Cmax and AUC of ruxolitinib decreased 32% and 61%, respectively, with the oral administration of 50 mg single dose of ruxolitinib following rifampin 600 mg once daily for 10 days, compared to receiving the oral ruxolitinib dose alone in healthy subjects.

In Vitro Studies

- Cytochrome P450 (CYP) Enzymes:Ruxolitinib is not expected to inhibit CYP1A2, 2B6, 2C8, 2C9, 2C19, 2D6 and CYP3A4 or induce CYP1A2, 2B6 and 3A4 following topical application.
- Transporter Systems:Ruxolitinib is not expected to inhibit P-gp, BCRP, OATP1B1, OATP1B3, OCT1, OCT2, OAT1, or OAT3 transporter systems following topical application. Ruxolitinib is not a substrate for the P-gp transporter.

13 NONCLINICAL TOXICOLOGY

13.1 Carcinogenesis, Mutagenesis, Impairment of Fertility

Ruxolitinib was not carcinogenic when administered orally in the 6-month Tg.rasH2 transgenic mouse model. In a 2-year oral rat carcinogenicity study, no drug-related tumors were observed at oral doses of ruxolitinib up to 60 mg/kg/day (3.5 times the MRHD clinical systemic exposure). In a 2-year dermal mouse carcinogenicity study, no drug-related tumors were observed at topical doses of ruxolitinib cream up to 1.5% applied at 100 μl/day (2.8 times the MRHD clinical systemic exposure).

Ruxolitinib was not mutagenic in a bacterial mutagenicity assay (Ames test) or clastogenic in an in vitro chromosomal aberration assay (cultured human peripheral blood lymphocytes) or an in vivo rat bone marrow micronucleus assay.

In a fertility study, ruxolitinib was administered orally to male rats prior to and throughout mating and to female rats prior to mating and up to the implantation day (gestation day 7). Ruxolitinib had no effect on fertility or reproductive function in male or female rats at doses up to 60 mg/kg/day (22 times the MRHD clinical systemic exposure). However, in female rats, doses of greater than or equal to 30 mg/kg/day (3.5 times the MRHD clinical systemic exposure) resulted in increased post-implantation loss.

14 CLINICAL STUDIES

14.1 Atopic Dermatitis

Adult and Pediatric Subjects 12 Years of Age and Older

Two double-blind, randomized, vehicle-controlled trials of identical design (TRuE-AD1 and TRuE-AD2, NCT03745638 and NCT03745651, respectively) enrolled a total of 1249 adult and pediatric subjects aged 12 and older, and subjects were treated twice daily (BID) for 8 weeks. A total of 20% of subjects were 12 to 17 years of age and 9% were 65 years or older. Females constituted 62% of subjects, 70% of subjects were White, 23% were Black, 4% were Asian, and 3% were other races. Subjects had affected body surface area (BSA) of 3 to 20%, and an Investigator’s Global Assessment (IGA) score of 2 (mild) to 3 (moderate) on a severity scale of 0 to 4. At baseline, subjects had a mean affected BSA of 9.8% and 39% had affected areas on the face, 25% of subjects had an IGA score of 2 and 75% had a score of 3. The baseline Itch Numerical Rating Scale (Itch NRS), defined as the 7-day average of the worst level of itch intensity in the last 24 hours, was 5 on a scale of 0 to 10.

The primary efficacy endpoint was the proportion of subjects at Week 8 achieving IGA treatment success (IGA-TS) defined as a score of 0 (clear) or 1 (almost clear) with ≥ 2 grade improvement from baseline. Efficacy was also assessed using a ≥ 4-point improvement in Itch NRS.

Efficacy results for OPZELURA from the two trials are summarized in Table 4.

Table 4: Efficacy Results at Week 8 in Adult and Pediatric Subjects 12 Years of Age and Older with Atopic Dermatitis (TRuE-AD1 and TRuE-AD2)
 | TRuE-AD1 |  |  | TRuE-AD2
 | OPZELURA (N = 253) | Vehicle (N = 126) | Treatment Difference and 95% Confidence Interval | OPZELURA (N = 228) | Vehicle (N = 118) | Treatment Difference and 95% Confidence Interval
IGA-TS [Defined as an IGA score of 0 or 1 with a ≥ 2-grade improvement from baseline] | 53.8% (136/253) | 15.1% (19/126) | 38.9% (30.3%, 47.4%) | 51.3% (117/228) | 7.6% (9/118) | 44.1% (36.2%, 52.0%)
Itch NRS (≥ 4 point reduction) (n/N) [N = subjects with a baseline Itch NRS score ≥ 4.] | 52.2% (84/161) | 15.4% (12/78) | 36.7% (25.5%, 48.0%) | 50.7% (74/146) | 16.3% (13/80) | 35.8% (24.4%, 47.2%)

Pediatric Subjects 2 to 11 Years of Age

A double-blind, randomized, vehicle-controlled trial, TRuE-AD3 (NCT04921969), enrolled a total of 330 pediatric subjects, 2 to 11 years of age, and subjects were treated twice daily (BID) for 8 weeks. In the trial, 51% of subjects were 2 to 6 years of age and 49% of subjects were 7 to 11 years of age. Females constituted 54% of subjects, 55% of subjects were White, 32% were Black, 6% were Asian, and 7% were other races. Subjects had affected BSA of 3 to 20%, and an IGA score of 2 (mild) to 3 (moderate) on a severity scale of 0 to 4. At baseline, subjects had a mean affected BSA of 10%, 24% of subjects had an IGA score of 2 and 76% of subjects had a score of 3.

The primary efficacy endpoint was the proportion of subjects at Week 8 achieving IGA treatment success (IGA-TS) defined as a score of 0 (clear) or 1 (almost clear) with ≥ 2 grade improvement from baseline. Efficacy results for OPZELURA from TRuE-AD3 are summarized in Table 5.

Table 5: Efficacy Results at Week 8 in Pediatric Subjects 2 to 11 Years of Age with Atopic Dermatitis (TRuE-AD3)
 | OPZELURA (N = 131) | Vehicle (N = 65) | Treatment Difference and 95% Confidence Interval
IGA-TS [Defined as an IGA score of 0 or 1 with a ≥ 2-grade improvement from baseline.] | 56.5% | 10.8% | 45.7%; (34.7%, 56.8%)

14.2 Nonsegmental Vitiligo

Two double-blind, randomized, vehicle-controlled trials of identical design (TRuE‑V1 and TRuE‑V2, NCT04052425 and NCT04057573, respectively) enrolled a total of 674 adult and pediatric subjects aged 12 years and older (11% of subjects were 12 to 17 years of age and 7% were 65 years or older). Females constituted 53% of subjects, 82% of subjects were White, 5% were Black, 4% were Asian, and 9% were other races. Fitzpatrick skin types included I (2%), II (30%), III (40%), IV (19%), V (7%), or VI (2%). Subjects had depigmented areas affecting ≥ 0.5% facial body surface area (F-BSA), ≥ 3% non-facial BSA, and total body vitiligo area (facial and non-facial, including hands, feet, upper and lower extremities, and trunk body areas) of up to 10% BSA. At baseline, subjects had a mean affected F-BSA of 1% and a mean affected total BSA of 7.4%. Phototherapy was not permitted during the trial. The mean time since diagnosis of nonsegmental vitiligo was 14.8 years prior to subjects enrolling in the trials.

In both trials, subjects were randomized 2:1 to treatment with OPZELURA or vehicle cream twice daily (BID) for 24 weeks followed by an additional 28 weeks of treatment with OPZELURA BID for all subjects. Lesions on the face were assessed with the facial Vitiligo Area Scoring Index (F-VASI) and lesions on the total body (including the face) were assessed with the total body Vitiligo Area Scoring Index (T-VASI). The primary efficacy endpoint was the proportion of subjects achieving at least 75% improvement in F-VASI (F-VASI75) at Week 24. The proportion of participants achieving at least 90% improvement in F-VASI (F-VASI90) was also evaluated.

Efficacy results for OPZELURA at Week 24 from the two trials are summarized in Table 6. The percentage of subjects who achieved F-VASI75 and T-VASI75 (at least 75% improvement in T‑VASI) over the 52-week treatment period in both trials are shown in Figure 1 and Figure 2.

Table 6: Efficacy Results at Week 24 in Adult and Pediatric Subjects Aged 12 Years and Older with Nonsegmental Vitiligo (TRuE-V1 and TRuE-V2)
 | TRuE-V1 |  |  | TRuE-V2
 | OPZELURA (N = 221) | Vehicle (N = 109) | Treatment Difference and 95% Confidence Interval | OPZELURA (N = 229) | Vehicle (N = 115) | Treatment Difference and 95% Confidence Interval
F-VASI75 | 29.9% | 7.5% | 22.5% (14.2%, 30.8%) | 29.9% | 12.9% | 16.9% (7.8%, 26.0%)
F-VASI90 | 15.5% | 2.2% | 13.3% (7.5%, 19.1%) | 15.4% | 1.9% | 13.5% (7.7%, 19.3%)

16 HOW SUPPLIED/STORAGE AND HANDLING

How Supplied

OPZELURA is a white to off-white cream containing 1.5% ruxolitinib and is supplied in 60 g and 100 g tubes.

60 g tube: NDC 50881-007-05

100 g tube: NDC 50881-007-07

Storage and Handling

Store OPZELURA at 20ºC to 25ºC (68ºF to 77ºF); excursions permitted from 15ºC to 30ºC (59ºF to 86ºF) [see USP Controlled Room Temperature].

17 PATIENT COUNSELING INFORMATION

Advise the patient or caregivers to read the FDA-approved patient labeling (Medication Guide).

Infections

Inform patients that they may be at increased risk for developing infections, including serious infections, when taking Janus kinase inhibitors. Instruct patients to tell their healthcare provider if they develop any signs or symptoms of an infection [see Warnings and Precautions (5.1)].

Advise patients that Janus kinase inhibitors increase the risk of herpes zoster, and some cases can be serious [see Warnings and Precautions (5.1)].

Malignancies and Lymphoproliferative Disorders

Inform patients that Janus kinase inhibitors may increase the risk for developing lymphomas and other malignancies including skin cancer [see Warnings and Precautions (5.3)].

Instruct patients to inform their health care provider if they have ever had any type of cancer. Inform patients that periodic skin examinations should be performed while using OPZELURA. Advise patients that exposure to sunlight, and UV light should be limited by wearing protective clothing and using a broad-spectrum sunscreen [see Warnings and Precautions (5.3)].

Major Adverse Cardiovascular Events

Advise patients that events of major adverse cardiovascular events (MACE) including non-fatal myocardial infarction, non-fatal stroke, and cardiovascular death, have been reported in clinical studies with Janus kinase inhibitors used to treat inflammatory conditions. Instruct all patients, especially current or past smokers or patients with other cardiovascular risk factors, to be alert for the development of signs and symptoms of cardiovascular events [see Warnings and Precautions (5.4)].

Thrombosis

Advise patients that events of DVT and PE have been reported in clinical studies with Janus kinase inhibitors used to treat inflammatory conditions. Instruct patients to tell their healthcare provider if they develop any signs or symptoms of a DVT or PE [see Warnings and Precautions (5.5)].

Cytopenias

Advise patients of the risk of thrombocytopenia, anemia, neutropenia, lymphopenia, and leukopenia with OPZELURA. Instruct patients to tell their healthcare provider if they develop any signs or symptoms of thrombocytopenia, anemia, neutropenia, lymphopenia, or leukopenia [see Warnings and Precautions (5.6)].

Administration Instructions

Advise patients or caregivers that OPZELURA is for topical use only [see Dosage and Administration (2.1,2.2)].

Atopic Dermatitis

- Adult and Pediatric Patients 12 Years of Age and Older: Advise patients or caregivers to limit treatment to one 60 gram tube of OPZELURA per week or one 100 gram tube per 2 weeks [see Dosage and Administration (2.1)].
- Pediatric Patients 2 to 11 Years of Age: Advise patients or caregivers to limit treatment to one 60 gram tube of OPZELURA per 2 weeks [see Dosage and Administration (2.1)].

Nonsegmental Vitiligo

- Advise patients or caregivers to limit treatment to one 60 gram tube of OPZELURA per week or one 100 gram tube per 2 weeks [see Dosage and Administration (2.2)].

Pregnancy Registry

Inform patients to report their pregnancy to Incyte Corporation at 1-855-463-3463 or by visiting www.opzelura.pregnancy.incyte.com [see Use in Specific Populations (8.1)].

Lactation

Advise a patient not to breastfeed during treatment with OPZELURA and for about four weeks after the last dose [see Use in Specific Populations (8.2)].

Manufactured for:
Incyte Corporation
1801 Augustine Cut-off
Wilmington, DE 19803

OPZELURA is a registered trademark of Incyte. All rights reserved.
Patent Information: www.incyte.com/patents
© 2021-2025 Incyte Corporation. All rights reserved.

MEDICATION GUIDE
OPZELURA® (OP-zuh-LUR-ah)
(ruxolitinib) cream

Important: OPZELURA is for use on the skin only. Do not use OPZELURA in your eyes, mouth, or vagina.

What is the most important information I should know about OPZELURA?

OPZELURA may cause serious side effects, including:

- Serious Infections. OPZELURA contains ruxolitinib. Ruxolitinib belongs to a class of medicines called Janus kinase (JAK) inhibitors. JAK inhibitors are medicines that affect your immune system. JAK inhibitors can lower the ability of your immune system to fight infections. Some people have had serious infections while taking JAK inhibitors by mouth, including tuberculosis (TB), and infections caused by bacteria, fungi, or viruses that can spread throughout the body. Some people have been hospitalized or died from these infections. Some people have had serious infections of their lungs while using OPZELURA.
  - Your healthcare provider should watch you closely for signs and symptoms of TB during treatment with OPZELURA.

OPZELURA should not be used in people with an active, serious infection, including localized infections. You should not start using OPZELURA if you have any kind of infection unless your healthcare provider tells you it is okay. You may be at a higher risk of developing shingles (herpes zoster) while using OPZELURA.

Before starting OPZELURA, tell your healthcare provider if you:

- are being treated for an infection
- have had an infection that does not go away or that keeps coming back
- have diabetes, chronic lung disease, HIV, or a weak immune system
- have TB or have been in close contact with someone with TB
- have had shingles (herpes zoster)
- have or have had hepatitis B or C
- live in an area, or have lived in an area, or have traveled to certain parts of the country (such as the Ohio and Mississippi River valleys and the Southwest) where there is an increased chance for getting certain kinds of fungal infections. These infections may happen or become more severe if you use OPZELURA. Ask your healthcare provider if you do not know if you have lived in an area where these infections are common.
- think you have an infection or have symptoms of an infection such as:

- fever, sweating, or chills
- muscle aches
- cough or shortness of breath

- blood in your phlegm
- weight loss
- warm, red, or painful skin or sores on your body

- diarrhea or stomach pain
- burning when you urinate or urinating more often than usual
- feeling very tired

After starting OPZELURA, call your healthcare provider right away if you have any symptoms of an infection.
OPZELURA can make you more likely to get infections or make worse any infections that you have. If you get a serious infection, your healthcare provider may stop your treatment with OPZELURA until your infection is controlled.

- Increased risk of death due to any reason (all causes). Increased risk of death has happened in people 50 years of age and older who have at least 1 heart disease (cardiovascular) risk factor and are taking a medicine in the class of medicines called JAK inhibitors by mouth.
- Cancer and immune system problems. OPZELURA may increase your risk of certain cancers by changing the way your immune system works.
  - Lymphoma and other cancers have happened in people taking a medicine in the class of medicines called JAK inhibitors by mouth.
  - People taking JAK inhibitors by mouth have a higher risk of certain cancers including lymphoma and lung cancer, especially if they are a current or past smoker.
  - Some people have had skin cancers while using OPZELURA. Your healthcare provider will regularly check your skin during your treatment with OPZELURA. Limit the amount of time you spend in the sunlight. Wear protective clothing when you are in the sun and use a broad-spectrum sunscreen.
  - Tell your healthcare provider if you have ever had any type of cancer.

- Increased risk of major cardiovascular events. Increased risk of major cardiovascular events such as heart attack, stroke, or death have happened in people 50 years of age and older who have at least 1 heart disease (cardiovascular) risk factor and taking a medicine in the class of medicines called JAK inhibitors by mouth, especially in current or past smokers.

Get emergency help right away if you have any symptoms of a heart attack or stroke while using OPZELURA, including:

- discomfort in the center of your chest that lasts for more than a few minutes, or that goes away and comes back
- severe tightness, pain, pressure, or heaviness in your chest, throat, neck, or jaw
- pain or discomfort in your arms, back, neck, jaw, or stomach
- shortness of breath with or without chest discomfort
- breaking out in a cold sweat
- nausea or vomiting
- feeling lightheaded
- weakness in one part or on one side of your body
- slurred speech

- Blood clots. Blood clots in the veins of your legs (deep vein thrombosis, DVT) or lungs (pulmonary embolism, PE) can happen in some people taking OPZELURA. This may be life-threatening. DVT and PE have happened more often in people who are 50 years of age and older and with at least 1 heart disease (cardiovascular) risk factor taking a medicine in the class of medicines called JAK inhibitors by mouth.
  - Tell your healthcare provider if you have had blood clots in the veins of your legs or lungs in the past.
  - Tell your healthcare provider right away if you have any signs and symptoms of blood clots during treatment with OPZELURA, including:
    - swelling, pain, or tenderness in one or both legs
    - sudden, unexplained chest or upper back pain
    - shortness of breath or difficulty breathing

See “What are the possible side effects of OPZELURA?” for more information about side effects.

What is OPZELURA?

OPZELURA is a prescription medicine used on the skin (topical) for:

- short-term and non-continuous chronic treatment of mild to moderate eczema (atopic dermatitis) in non‑immunocompromised adults and children 2 years of age and older whose disease:
  - is not well controlled with topical prescription therapies or
  - when those therapies are not recommended.

- the treatment of a type of vitiligo called nonsegmental vitiligo in adults and children 12 years of age and older.

The use of OPZELURA along with therapeutic biologics, other JAK inhibitors, or strong immunosuppressants such as azathioprine or cyclosporine is not recommended.

It is not known if OPZELURA is safe and effective in children less than 2 years of age with atopic dermatitis or in children less than 12 years of age with nonsegmental vitiligo.

Before using OPZELURA, tell your healthcare provider about all of your medical conditions, including if you:

- See “What is the most important information I should know about OPZELURA?”
- have an infection
- are a current or past smoker
- have had a heart attack, other heart problems, or a stroke
- have or have had low white or red blood cell counts
- have high levels of fat in your blood (high cholesterol or triglycerides)
- are pregnant or plan to become pregnant. It is not known if OPZELURA will harm your unborn baby.
  - Pregnancy Exposure Registry. There is a pregnancy exposure registry for individuals who use OPZELURA during pregnancy. The purpose of this registry is to collect information about the health of you and your baby. If you become exposed to OPZELURA during pregnancy, you and your healthcare provider should report exposure to Incyte Corporation at 1-855-463-3463 or by visiting www.opzelura.pregnancy.incyte.com.
- are breastfeeding or plan to breastfeed. It is not known if OPZELURA passes into your breast milk. Do not breastfeed during treatment with OPZELURA and for about 4 weeks after the last dose.

Tell your healthcare provider about all the medicines you take, including prescription and over-the-counter medicines, vitamins, and herbal supplements.

Know the medicines you take. Keep a list of them to show your healthcare provider and pharmacist when you get a new medicine.

How should I use OPZELURA?

- OPZELURA is for use on the skin only. Do not use OPZELURA in your eyes, mouth, or vagina.
- Use OPZELURA exactly as your healthcare provider tells you.
- Apply a thin layer of OPZELURA 2 times a day to affected areas.
- If you are using OPZELURA for atopic dermatitis:
  - Do not use OPZELURA with tight bandages that cover and seal the skin (occlusive dressings).
  - Adults and children 12 years of age and older:
    Do not use more than one 60 gram tube each week or more than one 100 gram tube every 2 weeks.
  - Children ages 2 to 11 years of age:
    Do not use more than one 60 gram tube every 2 weeks.
  - Ask your healthcare provider if you have questions about applying OPZELURA.
  - Stop using OPZELURA when your signs and symptoms of atopic dermatitis, such as itching, rash, and redness go away, or as directed by your healthcare provider. Tell your healthcare provider if your symptoms do not improve within 8 weeks of treatment.
- If you are using OPZELURA for nonsegmental vitiligo:
  - Do not use more than one 60 gram tube each week or more than one 100 gram tube every 2 weeks.
  - Tell your healthcare provider if your treated skin does not improve within 24 weeks of treatment.
- Wash your hands after applying OPZELURA, unless hands are being treated. If someone else applies OPZELURA, they should wash their hands after applying OPZELURA.

What are the possible side effects of OPZELURA?

OPZELURA may cause serious side effects, including:

- See “What is the most important information I should know about OPZELURA?”
- Low blood cell counts. OPZELURA may cause low platelet counts (thrombocytopenia), low red blood cell counts (anemia), and low white blood cell counts (neutropenia). If needed, your healthcare provider will do a blood test to check your blood cell counts during your treatment with OPZELURA and may stop your treatment if signs or symptoms of low blood cell counts happen. Tell your healthcare provider right away if you develop or have worsening of any of these symptoms:

- unusual bleeding
- bruising
- tiredness

- shortness of breath
- fever

- Cholesterol increases. Cholesterol increase has happened in people when ruxolitinib is taken by mouth. Tell your healthcare provider if you have high levels of fat in your blood (high cholesterol or triglycerides).

The most common side effects of OPZELURA in people treated for atopic dermatitis include:

- common cold (nasopharyngitis)
- diarrhea
- bronchitis
- ear infection
- increase in a type of white blood cell (eosinophil) count or decrease in a type of white blood cell (neutropenia) count

- hives
- inflamed hair pores (folliculitis)
- swelling of the tonsils (tonsillitis)
- runny nose (rhinorrhea)
- upper respiratory tract infection
- COVID-19
- pain, irritation, discomfort, or itching at the application site
- fever

The most common side effects of OPZELURA in people treated for nonsegmental vitiligo include:

- acne at the application site
- itching at the application site
- common cold (nasopharyngitis)
- headache

- urinary tract infection
- redness at the application site
- fever

These are not all of the possible side effects of OPZELURA.

Call your doctor for medical advice about side effects. You may report side effects to FDA at 1‑800-FDA-1088.

You may also report side effects to Incyte Corporation at 1-855-463-3463.

How should I store OPZELURA?

- Store OPZELURA at room temperature between 68°F to 77°F (20°C to 25°C).

Keep OPZELURA and all medicines out of the reach of children.

General information about the safe and effective use of OPZELURA.

Medicines are sometimes prescribed for purposes other than those listed in a Medication Guide. Do not use OPZELURA for a condition for which it is not prescribed. Do not give OPZELURA to other people, even if they have the same symptoms you have. It may harm them. You can ask your pharmacist or healthcare provider for information about OPZELURA that is written for healthcare professionals.

What are the ingredients in OPZELURA?

Active ingredient: ruxolitinib phosphate
Inactive ingredients: cetyl alcohol, dimethicone 350, edetate disodium, glyceryl stearate SE, light mineral oil, medium chain triglycerides, methylparaben, phenoxyethanol, phosphoric acid, polyethylene glycol 200, polysorbate 20, propylene glycol, propylparaben, stearyl alcohol, purified water, white petrolatum, and xanthan gum.

Manufactured for: Incyte Corporation, 1801 Augustine Cut-off, Wilmington, DE 19803
OPZELURA is a registered trademark of Incyte. All rights reserved.
Patent Information: www.incyte.com/patents

For more information go to www.Opzelura.com or call 1-855-463-3463

This Medication Guide has been approved by the U.S. Food and Drug Administration. Revised: 09/2025

100 g Carton Label

Opzelura®
(ruxolitinib) cream 1.5%

For Topical Use Only.

NDC 50881-007-07

100 g
Rx only

100 g Tube Label

Opzelura®
(ruxolitinib) cream 1.5%

For Topical Use Only.

NDC 50881-007-07

100 g
Rx only

60 g Carton Label

Opzelura®
(ruxolitinib) cream 1.5%

For Topical Use Only.

NDC 50881-007-05

60 g
Rx only

60 g Tube Label

Opzelura®
(ruxolitinib) cream 1.5%

For Topical Use Only.

NDC 50881-007-05

60 g
Rx only

5 g Carton Label - Sample

Opzelura®
(ruxolitinib) cream 1.5%

Sample - Topical Use Only.

NDC 50881-007-04

5 g
Rx only

5 g Tube Label - Sample

Opzelura®
(ruxolitinib) cream 1.5%

Sample - Topical Use Only.

NDC 50881-007-04

5 g
Rx only

3 g Carton Label - Sample

Opzelura®
(ruxolitinib) cream 1.5%

Sample - Topical Use Only.

NDC 50881-007-14

3 g
Rx only

3 g Tube Label - Sample

Opzelura®
(ruxolitinib) cream 1.5%

Sample - Topical Use Only.

NDC 50881-007-14

3 g
Rx only